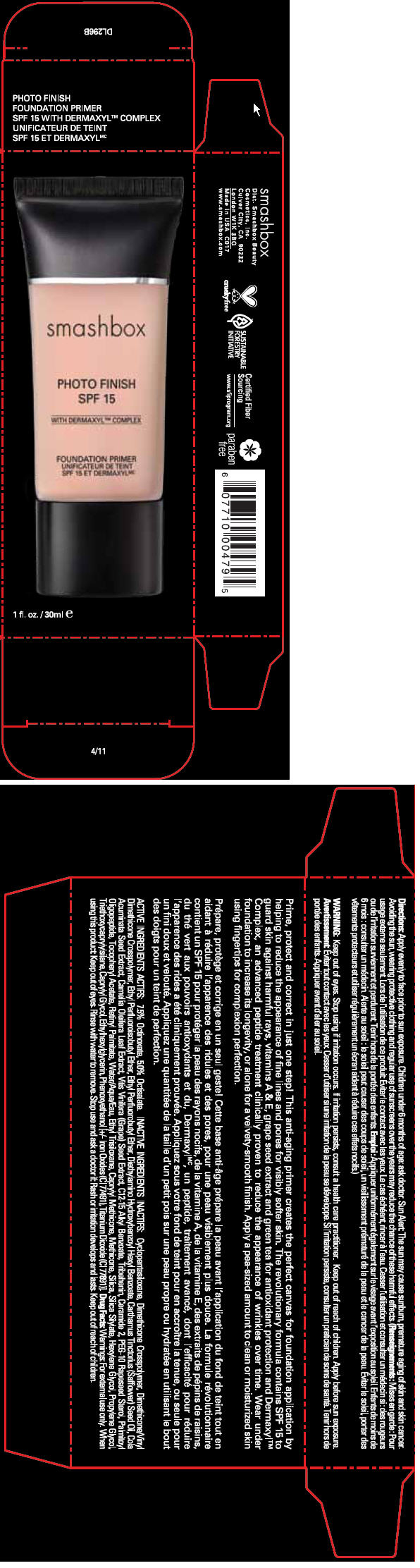 DRUG LABEL: smashbox 
NDC: 10348-004 | Form: LOTION
Manufacturer: SMASHBOX  BEAUTY COSMETICS, INC
Category: otc | Type: HUMAN OTC DRUG LABEL
Date: 20120123

ACTIVE INGREDIENTS: OCTINOXATE 7.5 mL/100 mL; OCTISALATE 5 mL/100 mL
INACTIVE INGREDIENTS: Cyclomethicone 5; Diethylamino Hydroxybenzoyl Hexyl Benzoate; Safflower Oil; Cola Acuminata Seed; Camellia Oleifera Leaf; Vitis Vinifera Seed; Alkyl (C12-15) Benzoate; Tribehenin; Ceramide 2; PEG-10 Rapeseed Sterol; Palmitoyl Oligopeptide; Alpha-Tocopherol Acetate; Vitamin A Palmitate; Water; Silicon Dioxide; Hexylene Glycol; Propylene Glycol; Triethoxycaprylylsilane; Caprylyl Glycol; Ethylhexylglycerin; Phenoxyethanol; Ferric Oxide Red; Titanium Dioxide

smashbox
PHOTO FINISH SPF 15 FOUNDATION PRIMER

Directions

Apply evenly to face prior to sun exposure. Children under 6 months of age: ask doctor.

Sun Alert

The sun may cause sunburn, premature aging of skin and skin cancer. Avoiding the sun, wearing protective clothing and regular use of sunscreens over the years may reduce the chance of these harmful effects.

WARNING

Keep out of eyes.

Stop using if irritation occurs.

ASK DOCTOR

If irritation persists, consult a health care practitioner.

Keep out of reach of children.

Apply before sun exposure.

ACTIVE INGREDIENTS

7.5% Octinoxate, 5.0% Octisalate.

INACTIVE INGREDIENTS

Cyclopentasiloxane, Dimethicone Crosspolymer, Dimethicone/Vinyl Dimethicone Crosspolymer, Ethyl Perfluoroisobutyl Ether, Ethyl Perfluorobutyl Ether, Diethylamino Hydroxybenzoyl Hexyl Benzoate, Carthamus Tinctorius (Safflower) Seed Oil, Cola Acuminata Seed Extract, Camellia Oleifera Leaf Extract, Vitis Vinifera (Grape) Seed Extract, C12-15 Alkyl Benzoate, Tribehenin, Ceramide 2, PEG-10 Rapeseed Sterol, Palmitoyl Oligopeptide, Tocophenyl Acetate, Retinyl Palmitate, Water/Aqua/Eau, Ethyl Trisiloxane, Caprylyl Methicone, Methicone, Silica, Silica Silylate, Hexylene Glycol, Propylene Glycol, Triethoxycaprylylsilane, Caprylyl Glycol, Ethylhexylglycerin, Phenoxyethanol [+/- Iron Oxides (CI77491), Titanium Dioxide (CI77891)].

Drug Facts

Warnings

For external use only.

When using this product

Keep out of eyes. Rinse with water to remove.

STOP USE

Stop use and ask a doctor if

Rash or irritation develops and lasts.

Keep out of reach of children.

Dist. Smashbox Beauty
Cosmetics, Inc.
Culver City, CA 90232

PRINCIPAL DISPLAY PANEL - 30 ml Tube Carton

smashbox

PHOTO FINISH
SPF 15

WITH DERMAXYL™ COMPLEX

FOUNDATION PRIMER
SPF 15 ET DERMAXYL™

1 fl. oz./30ml e